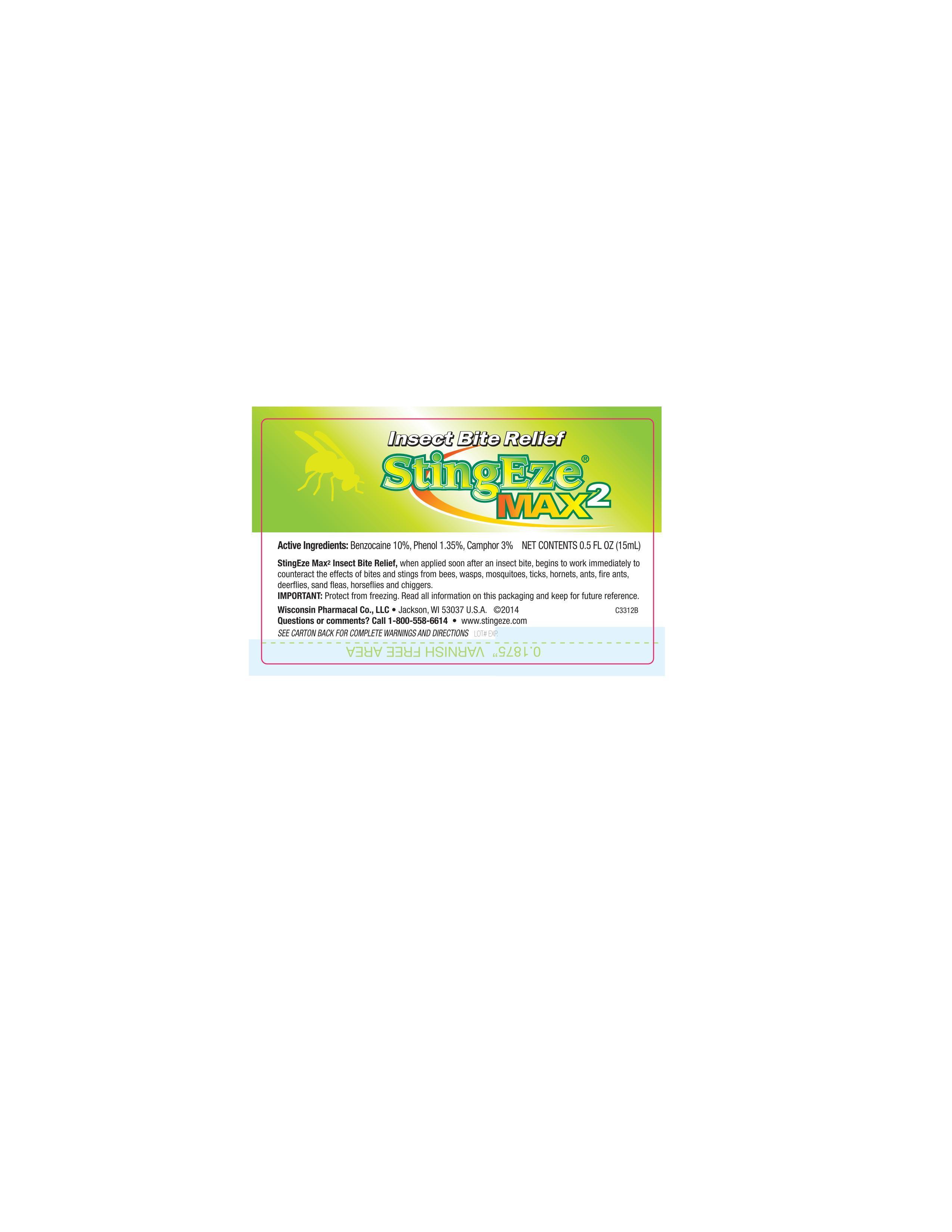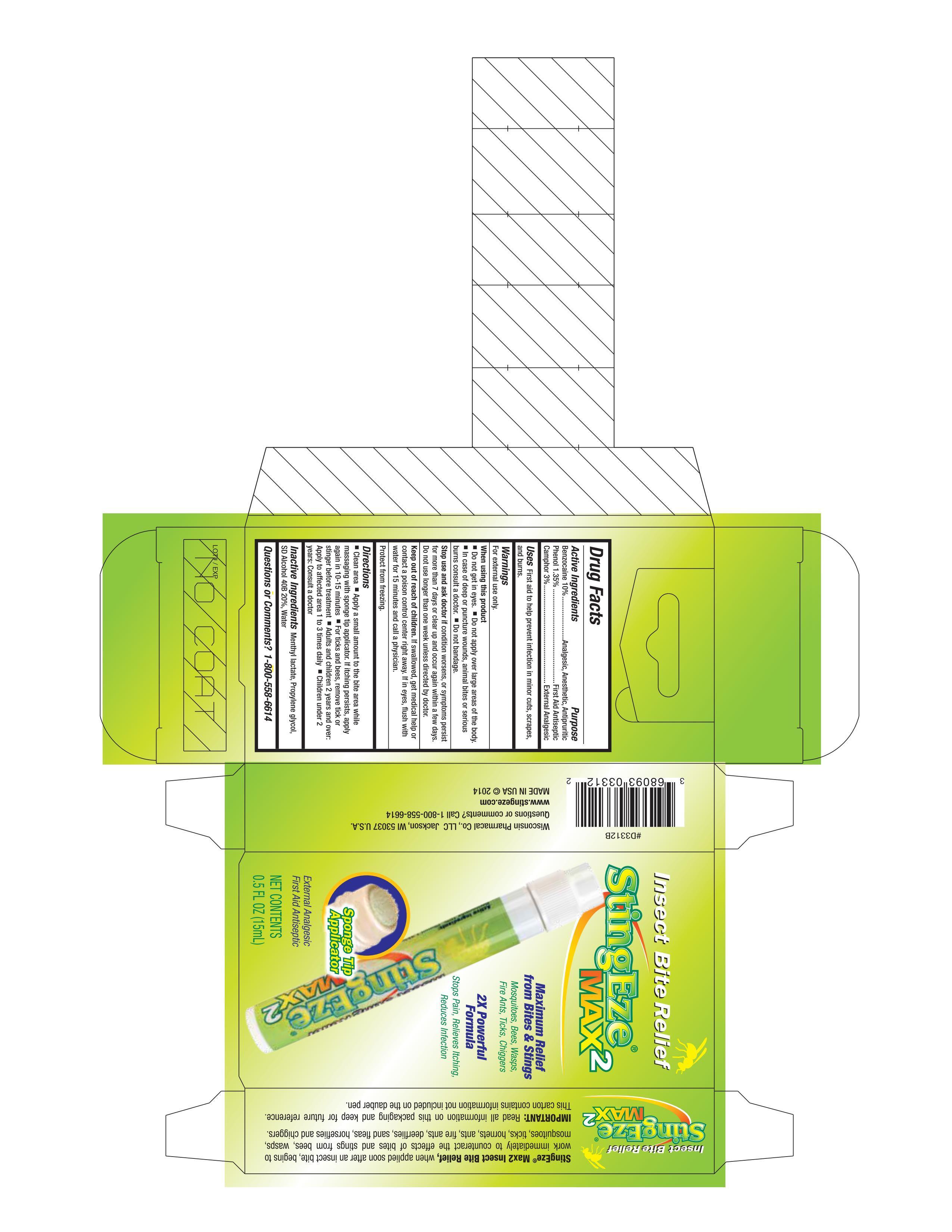 DRUG LABEL: StingEze
NDC: 68093-7151 | Form: LIQUID
Manufacturer: Wisconsin Pharmacal Company
Category: otc | Type: HUMAN OTC DRUG LABEL
Date: 20131223

ACTIVE INGREDIENTS: Benzocaine 0.10 g/1 g; Phenol 0.0135 g/1 g; CAMPHOR (SYNTHETIC) 0.03 g/1 g
INACTIVE INGREDIENTS: Propylene Glycol; Menthyl Lactate, (-)-; Alcohol; Water

Drug Facts

Drug Facts

Active Ingredients

Benzocaine 10%

Phenol 1.35%

Camphor 3%

Purpose

Analgesic, Anesthetic, Antipuritic

First Aid Antiseptic

External Analgesic

Uses

First aid to help prevent infection in minor cuts, scrapes, and burns.

Warnings

For external use only.

When using this product

- Do not get in eyes
- Do not apply over large areas of the body
- In case of deep or puncture wounds, animal bites, or serious burns consult a doctor
- Do not bandage.

Stop use and ask doctor if

condition worsens, or symptoms persist for more than 7 days or clear up and occur again within a few days. Do not use longer than one week unless directed by a doctor.

Keep out of reach of children.

If swallowed, get medical help or contact a poison control center right away. If in eyes, flush with water for 15 minutes and call a physician.

Directions

- Clean area
- Apply a small amount to the bite area while massaging with sponge tip applicator. If itching persists, apply again in 10-15 minutes
- For ticks and bees, remove tick or stinger before treatment
- Adults and children 2 years and over: Apply to affected area 1 to 3 times daily
- Children under 2 years: Consult a doctor

Inactive Ingredients

Camphor, Menthyl lactate, Propylene Glycol, SD Alcohol 40B 20%, Water

Questions or Comments?

1-800-558-6614

PACKAGE LABEL

Enter section text here